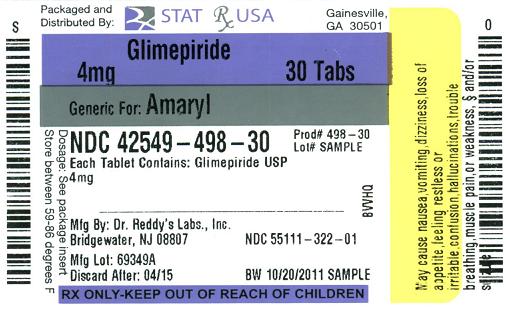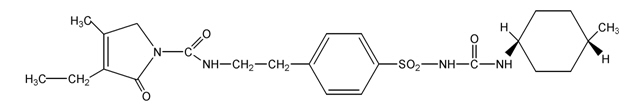 DRUG LABEL: GLIMEPIRIDE
NDC: 42549-498 | Form: TABLET
Manufacturer: STAT Rx USA LLC
Category: prescription | Type: HUMAN PRESCRIPTION DRUG LABEL
Date: 20120327

ACTIVE INGREDIENTS: GLIMEPIRIDE 4 mg/1 1
INACTIVE INGREDIENTS: LACTOSE MONOHYDRATE; MAGNESIUM STEARATE; CELLULOSE, MICROCRYSTALLINE; POVIDONE; SODIUM STARCH GLYCOLATE TYPE A POTATO; D&C YELLOW NO. 10; FD&C BLUE NO. 1

DESCRIPTION

Glimepiride tablets USP are an oral blood-glucose-lowering drug of the sulfonylurea class. Glimepiride is a white to yellowish-white, crystalline, odorless to practically odorless powder formulated into tablets of 1 mg, 2 mg, and 4 mg strengths for oral administration. Glimepiride tablets USP contain the active ingredient glimepiride and the following inactive ingredients: lactose monohydrate, magnesium stearate, microcrystalline cellulose, povidone, and sodium starch glycolate. In addition, glimepiride tablets USP 1 mg contain ferric oxide red, glimepiride tablets USP 2 mg contain ferric oxide yellow and FD&C Blue #2 aluminum lake, and glimepiride tablets USP 4 mg contain FD&C Blue #2 aluminum lake.

Chemically, glimepiride is identified as 1-[[p-[2-(3-ethyl-4-methyl-2-oxo-3-pyrroline-1-carboxamido)ethyl]phenyl]sulfonyl]-3-(trans-4-methylcyclohexyl)urea.

The CAS Registry Number is 93479-97-1

The structural formula is:

Molecular Formula: C24H34N4O5S

Molecular Weight: 490.62

Glimepiride is practically insoluble in water.

CLINICAL PHARMACOLOGY

Mechanism of Action

The primary mechanism of action of glimepiride in lowering blood glucose appears to be dependent on stimulating the release of insulin from functioning pancreatic beta cells. In addition, extrapancreatic effects may also play a role in the activity of sulfonylureas such as glimepiride. This is supported by both preclinical and clinical studies demonstrating that glimepiride administration can lead to increased sensitivity of peripheral tissues to insulin. These findings are consistent with the results of a long-term, randomized, placebo-controlled trial in which glimepiride therapy improved postprandial insulin/C-peptide responses and overall glycemic control without producing clinically meaningful increases in fasting insulin/C-peptide levels. However, as with other sulfonylureas, the mechanism by which glimepiride lowers blood glucose during long-term administration has not been clearly established.

Glimepiride is effective as initial drug therapy. In patients where monotherapy with glimepiride or metformin has not produced adequate glycemic control, the combination of glimepiride and metformin may have a synergistic effect, since both agents act to improve glucose tolerance by different primary mechanisms of action. This complementary effect has been observed with metformin and other sulfonylureas, in multiple studies.

Pharmacodynamics

A mild glucose-lowering effect first appeared following single oral doses as low as 0.5 to 0.6 mg in healthy subjects. The time required to reach the maximum effect (i.e., minimum blood glucose level [Tmin]) was about 2 to 3 hours. In noninsulin-dependent (Type 2) diabetes mellitus (NIDDM) patients, both fasting and 2 hour postprandial glucose levels were significantly lower with glimepiride (1, 2, 4, and 8 mg once daily) than with placebo after 14 days of oral dosing. The glucose-lowering effect in all active treatment groups was maintained over 24 hours.

In larger dose-ranging studies, blood glucose and HbA1c were found to respond in a dose-dependent manner over the range of 1 to 4 mg/day of glimepiride. Some patients, particularly those with higher fasting plasma glucose (FPG) levels, may benefit from doses of glimepiride up to 8 mg once daily. No difference in response was found when glimepiride was administered once or twice daily.

In two 14 week, placebo-controlled studies in 720 subjects, the average net reduction in HbA1c for glimepiride tablet patients treated with 8 mg once daily was 2.0% in absolute units compared with placebo-treated patients. In a long-term, randomized, placebo-controlled study of Type 2 diabetic patients unresponsive to dietary management, glimepiride therapy improved postprandial insulin/C-peptide responses, and 75% of patients achieved and maintained control of blood glucose and HbA1c. Efficacy results were not affected by age, gender, weight, or race.

In long-term extension trials with previously-treated patients, no meaningful deterioration in mean fasting blood glucose (FBG) or HbA1c levels was seen after 2½ years of glimepiride therapy.

Combination therapy with glimepiride and insulin (70% NPH/30% regular) was compared to placebo/insulin in secondary failure patients whose body weight was > 130% of their ideal body weight. Initially, 5 to 10 units of insulin were administered with the main evening meal and titrated upward weekly to achieve predefined FPG values. Both groups in this double-blind study achieved similar reductions in FPG levels but the glimepiride/insulin therapy group used approximately 38% less insulin.

Glimepiride therapy is effective in controlling blood glucose without deleterious changes in the plasma lipoprotein profiles of patients treated for Type 2 diabetes.

Pharmacokinetics

Absorption

After oral administration, glimepiride is completely (100%) absorbed from the GI tract. Studies with single oral doses in normal subjects and with multiple oral doses in patients with Type 2 diabetes have shown significant absorption of glimepiride within 1 hour after administration and peak drug levels (Cmax) at 2 to 3 hours. When glimepiride was given with meals, the mean Tmax (time to reach Cmax) was slightly increased (12%) and the mean Cmax and AUC (area under the curve) were slightly decreased (8% and 9%, respectively).

Distribution

After intravenous (IV) dosing in normal subjects, the volume of distribution (Vd) was 8.8 L (113 mL/kg), and the total body clearance (CL) was 47.8 mL/min. Protein binding was greater than 99.5%.

Metabolism

Glimepiride is completely metabolized by oxidative biotransformation after either an IV or oral dose. The major metabolites are the cyclohexyl hydroxy methyl derivative (M1) and the carboxyl derivative (M2). Cytochrome P450 2C9 has been shown to be involved in the biotransformation of glimepiride to M1. M1 is further metabolized to M2 by one or several cytosolic enzymes. M1, but not M2, possesses about 1/3 of the pharmacological activity as compared to its parent in an

animal model; however, whether the glucose-lowering effect of M1 is clinically meaningful is not clear.

Excretion

When ^14C-glimepiride was given orally, approximately 60% of the total radioactivity was recovered in the urine in 7 days and M1 (predominant) and M2 accounted for 80 to 90% of that recovered in the urine. Approximately 40% of the total radioactivity was recovered in feces and M1 and M2 (predominant) accounted for about 70% of that recovered in feces. No parent drug was recovered from urine or feces. After IV dosing in patients, no significant biliary excretion of glimepiride or its M1 metabolite has been observed.

Pharmacokinetic Parameters

The pharmacokinetic parameters of glimepiride obtained from a single-dose, crossover, dose-proportionality (1, 2, 4, and 8 mg) study in normal subjects and from a single- and multiple-dose, parallel, dose-proportionality (4 and 8 mg) study in patients with Type 2 diabetes are summarized below:

 | Volunteers | Patients With Type 2 Diabetes
 | Single Dose | Single Dose (Day 1) | Multiple Dose (Day 10)
 | Mean ± SD | Mean ± SD | Mean ± SD
Cmax (ng/mL)
1 mg | 103 ± 34 (12) | — | —
2 mg | 177 ± 44 (12) | — | —
4 mg | 308 ± 69 (12) | 352 ± 222 (12) | 309 ± 134 (12)
8 mg | 551 ± 152 (12) | 591 ± 232 (14) | 578 ± 265 (11)
Tmax (h) | 2.4 ± 0.8 (48) | 2.5 ± 1.2 (26) | 2.8 ± 2.2 (23)
CL/f (mL/min) | 52.1 ± 16.0 (48) | 48.5 ± 29.3 (26) | 52.7 ± 40.3 (23)
Vd/f (L) | 21.8 ± 13.9 (48) | 19.8 ± 12.7 (26) | 37.1 ± 18.2 (23)
T1/2 (h) | 5.3 ± 4.1 (48) | 5.0 ± 2.5 (26) | 9.2 ± 3.6 (23)

() = No. of subjects

CL/f = Total body clearance after oral dosing

Vd/f = Volume of distribution calculated after oral dosing

These data indicate that glimepiride did not accumulate in serum, and the pharmacokinetics of glimepiride were not different in healthy volunteers and in Type 2 diabetic patients. Oral clearance of glimepiride did not change over the 1 to 8 mg dose range, indicating linear pharmacokinetics.

Variability

In normal healthy volunteers, the intra-individual variabilities of Cmax, AUC, and CL/f for glimepiride were 23%, 17%, and 15%, respectively, and the inter-individual variabilities were 25%, 29%, and 24%, respectively.

Special Populations

Geriatric

Comparison of glimepiride pharmacokinetics in Type 2 diabetic patients ≤ 65 years and those > 65 years was performed in a study using a dosing regimen of 6 mg daily. There were no significant differences in glimepiride pharmacokinetics between the two age groups. The mean AUC at steady state for the older patients was about 13% lower than that for the younger patients; the mean weight-adjusted clearance for the older patients was about 11% higher than that for the younger patients.

Pediatric

The pharmacokinetics of glimepiride (1 mg) were evaluated in a single dose study conducted in 30 Type 2 diabetic patients (Male = 7; Female = 23) between ages 10 and 17 years. The mean AUC(0-last) (338.8±203.1 ng•hr/mL), Cmax (102.4±47.7 ng/mL) and T1/2 (3.1±1.7 hours) were comparable to those previously reported in adults (AUC(0-last) 315.2±95.9 ng•hr/mL, Cmax 103.2±34.3 ng/mL and T1/2 5.3±4.1 hours).

Gender

There were no differences between males and females in the pharmacokinetics of glimepiride when adjustment was made for differences in body weight.

Race

No pharmacokinetic studies to assess the effects of race have been performed, but in placebo-controlled studies of glimepiride tablets in patients with Type 2 diabetes, the antihyperglycemic effect was comparable in whites (n = 536), blacks (n = 63), and Hispanics (n = 63).

Renal Insufficiency

A single-dose, open-label study was conducted in 15 patients with renal impairment. Glimepiride (3 mg) was administered to 3 groups of patients with different levels of mean creatinine clearance (CLcr); (Group I, CLcr = 77.7 mL/min, n = 5), (Group II, CLcr = 27.7 mL/min, n = 3), and (Group III, CLcr = 9.4 mL/min, n = 7). Glimepiride was found to be well tolerated in all 3 groups. The results showed that glimepiride serum levels decreased as renal function decreased. However, M1 and M2 serum levels (mean AUC values) increased 2.3 and 8.6 times from Group I to Group III. The apparent terminal half-life (T1/2) for glimepiride did not change, while the half-lives for M1 and M2 increased as renal function decreased. Mean urinary excretion of M1 plus M2 as percent of dose, however, decreased (44.4%, 21.9%, and 9.3% for Groups I to III).

A multiple-dose titration study was also conducted in 16 Type 2 diabetic patients with renal impairment using doses ranging from 1 to 8 mg daily for 3 months. The results were consistent with those observed after single doses. All patients with a CLcr less than 22 mL/min had adequate control of their glucose levels with a dosage regimen of only 1 mg daily. The results from this study suggested that a starting dose of 1 mg glimepiride may be given to Type 2 diabetic patients with kidney disease, and the dose may be titrated based on fasting blood glucose levels.

Hepatic Insufficiency

No studies were performed in patients with hepatic insufficiency.

Other Populations

There were no important differences in glimepiride metabolism in subjects identified as phenotypically different drug-metabolizers by their metabolism of sparteine.

The pharmacokinetics of glimepiride in morbidly obese patients were similar to those in the normal weight group, except for a lower Cmax and AUC. However, since neither Cmax nor AUC values were normalized for body surface area, the lower values of Cmax and AUC for the obese patients were likely the result of their excess weight and not due to a difference in the kinetics of glimepiride.

Drug Interactions

The hypoglycemic action of sulfonylureas may be potentiated by certain drugs, including non-steroidal anti-inflammatory drugs, clarithromycin, disopyramide, fluoxetine, and quinolones and other drugs that are highly protein bound, such as salicylates, sulfonamides, chloramphenicol, coumarins, probenecid, monoamine oxidase inhibitors, and beta adrenergic blocking agents. When these drugs are administered to a patient receiving glimepiride, the patient should be observed closely for hypoglycemia. When these drugs are withdrawn from a patient receiving glimepiride, the patient should be observed closely for loss of glycemic control.

A potential interaction between oral miconazole and oral hypoglycemic agents leading to severe hypoglycemia has been reported. Whether this interaction also occurs with the intravenous, topical, or vaginal preparations of miconazole is not known.

Certain drugs tend to produce hyperglycemia and may lead to loss of control. These drugs include the thiazides and other diuretics, corticosteroids, phenothiazines, thyroid products, estrogens, oral contraceptives, phenytoin, nicotinic acid, sympathomimetics, and isoniazid. When these drugs are administered to a patient receiving glimepiride, the patient should be closely observed for loss of control. When these drugs are withdrawn from a patient receiving glimepiride, the patient should be observed closely for hypoglycemia.

Coadministration of aspirin (1 g tid) and glimepiride led to a 34% decrease in the mean glimepiride AUC and, therefore, a 34% increase in the mean CL/f. The mean Cmax had a decrease of 4%. Blood glucose and serum C-peptide concentrations were unaffected and no hypoglycemic symptoms were reported. Pooled data from clinical trials showed no evidence of clinically significant adverse interactions with uncontrolled concurrent administration of aspirin and other salicylates.

Coadministration of either cimetidine (800 mg once daily) or ranitidine (150 mg bid) with a single 4 mg oral dose of glimepiride did not significantly alter the absorption and disposition of glimepiride, and no differences were seen in hypoglycemic symptomatology. Pooled data from clinical trials showed no evidence of clinically significant adverse interactions with uncontrolled concurrent administration of H2-receptor antagonists.

Concomitant administration of propranolol (40 mg tid) and glimepiride significantly increased Cmax, AUC, and T1/2 of glimepiride by 23%, 22%, and 15%, respectively, and it decreased CL/f by 18%. The recovery of M1 and M2 from urine, however, did not change. The pharmacodynamic responses to glimepiride were nearly identical in normal subjects receiving propranolol and placebo. Pooled data from clinical trials in patients with Type 2 diabetes showed no evidence of clinically significant adverse interactions with uncontrolled concurrent administration of beta-blockers. However, if beta-blockers are used, caution should be exercised and patients should be warned about the potential for hypoglycemia.

Concomitant administration of glimepiride tablets (4 mg once daily) did not alter the pharmacokinetic characteristics of R- and S-warfarin enantiomers following administration of a single dose (25 mg) of racemic warfarin to healthy subjects. No changes were observed in warfarin plasma protein binding. Glimepiride treatment did result in a slight, but statistically significant, decrease in the pharmacodynamic response to warfarin. The reductions in mean area under the prothrombin time (PT) curve and maximum PT values during glimepiride treatment were very small (3.3% and 9.9%, respectively) and are unlikely to be clinically important.

The responses of serum glucose, insulin, C-peptide, and plasma glucagon to 2 mg glimepiride were unaffected by coadministration of ramipril (an ACE inhibitor) 5 mg once daily in normal subjects. No hypoglycemic symptoms were reported. Pooled data from clinical trials in patients with Type 2 diabetes showed no evidence of clinically significant adverse interactions with uncontrolled concurrent administration of ACE inhibitors.

There is a potential interaction of glimepiride with inhibitors (e.g., fluconazole) and inducers (e.g., rifampicin) of cytochrome P450 2C9.

Although no specific interaction studies were performed, pooled data from clinical trials showed no evidence of clinically significant adverse interactions with uncontrolled concurrent administration of calcium-channel blockers, estrogens, fibrates, NSAIDS, HMG CoA reductase inhibitors, sulfonamides, or thyroid hormone.

INDICATIONS AND USAGE

Glimepiride tablets are indicated as an adjunct to diet and exercise to improve glycemic control in adults with type 2 diabetes mellitus (see DOSAGE AND ADMINISTRATION).

CONTRAINDICATIONS

Glimepiride tablets are contraindicated in patients with

1. Known hypersensitivity to the drug.
2. Diabetic ketoacidosis, with or without coma. This condition should be treated with insulin.

WARNINGS

SPECIAL WARNING ON INCREASED RISK OF CARDIOVASCULAR MORTALITY

The administration of oral hypoglycemic drugs has been reported to be associated with increased cardiovascular mortality as compared to treatment with diet alone or diet plus insulin. This warning is based on the study conducted by the University Group Diabetes Program (UGDP), a long-term, prospective clinical trial designed to evaluate the effectiveness of glucose-lowering drugs in preventing or delaying vascular complications in patients with non-insulin-dependent diabetes. The study involved 823 patients who were randomly assigned to one of four treatment groups (Diabetes, 19 supp. 2: 747-830, 1970).

UGDP reported that patients treated for 5 to 8 years with diet plus a fixed dose of tolbutamide (1.5 grams per day) had a rate of cardiovascular mortality approximately 2½ times that of patients treated with diet alone. A significant increase in total mortality was not observed, but the use of tolbutamide was discontinued based on the increase in cardiovascular mortality, thus limiting the opportunity for the study to show an increase in overall mortality. Despite controversy regarding the interpretation of these results, the findings of the UGDP study provide an adequate basis for this warning. The patient should be informed of the potential risks and advantages of glimepiride tablets and of alternative modes of therapy.

Although only one drug in the sulfonylurea class (tolbutamide) was included in this study, it is prudent from a safety standpoint to consider that this warning may also apply to other oral hypoglycemic drugs in this class, in view of their close similarities in mode of action and chemical structure.

Persons allergic to other sulfonamide derivatives may develop an allergic reaction to glimepiride as well.

PRECAUTIONS

General

Macrovascular Outcomes

There have been no clinical studies establishing conclusive evidence of macrovascular risk reduction with glimepiride or any other anti-diabetic drug.

Hypoglycemia

All sulfonylurea drugs are capable of producing severe hypoglycemia. Proper patient selection, dosage, and instructions are important to avoid hypoglycemic episodes. Patients with impaired renal function may be more sensitive to the glucose-lowering effect of glimepiride. A starting dose of 1 mg once daily followed by appropriate dose titration is recommended in those patients. Debilitated or malnourished patients, and those with adrenal, pituitary, or hepatic insufficiency are particularly susceptible to the hypoglycemic action of glucose-lowering drugs. Hypoglycemia may be difficult to recognize in patients with autonomic neuropathy, the elderly and in people who are taking beta-adrenergic blocking drugs or other sympatholytic agents. Hypoglycemia is more likely to occur when caloric intake is deficient, after severe or prolonged exercise, when alcohol is ingested, or when more than one glucose-lowering drug is used. Combined use of glimepiride with insulin or metformin may increase the potential for hypoglycemia.

Loss of Control of Blood Glucose

When a patient stabilized on any diabetic regimen is exposed to stress such as fever, trauma, infection, or surgery, a loss of control may occur. At such times, it may be necessary to add insulin in combination with glimepiride or even use insulin monotherapy. The effectiveness of any oral hypoglycemic drug, including glimepiride, in lowering blood glucose to a desired level decreases in many patients over a period of time, which may be due to progression of the severity of the diabetes or to diminished responsiveness to the drug. This phenomenon is known as secondary failure, to distinguish it from primary failure in which the drug is ineffective in an individual patient when first given. Should secondary failure occur with glimepiride or metformin monotherapy, combined therapy with glimepiride and metformin or glimepiride and insulin may result in a response. Should secondary failure occur with combined glimepiride/metformin therapy, it may be necessary to initiate insulin therapy.

Hemolytic Anemia

Treatment of patients with glucose 6-phosphate dehydrogenase (G6PD) deficiency with sulfonylurea agents can lead to hemolytic anemia. Since glimepiride belongs to the class of sulfonylurea agents, caution should be used in patients with G6PD deficiency and a non-sulfonylurea alternative should be considered. In postmarketing reports, hemolytic anemia has been reported in patients who did not have known G6PD deficiency.

Information for Patients

Patients should be informed of the potential risks and advantages of glimepiride and of alternative modes of therapy. They should also be informed about the importance of adherence to dietary instructions, of a regular exercise program, and of regular testing of blood glucose.

The risks of hypoglycemia, its symptoms and treatment, and conditions that predispose to its development should be explained to patients and responsible family members. The potential for primary and secondary failure should also be explained.

Laboratory Tests

Fasting blood glucose should be monitored periodically to determine therapeutic response. Glycosylated hemoglobin should also be monitored, usually every 3 to 6 months, to more precisely assess long-term glycemic control.

Drug Interactions

(See CLINICAL PHARMACOLOGY, Drug Interactions.)

Carcinogenesis, Mutagenesis, Impairment of Fertility

Studies in rats at doses of up to 5000 ppm in complete feed (approximately 340 times the maximum recommended human dose, based on surface area) for 30 months showed no evidence of carcinogenesis. In mice, administration of glimepiride for 24 months resulted in an increase in benign pancreatic adenoma formation which was dose related and is thought to be the result of chronic pancreatic stimulation. The no-effect dose for adenoma formation in mice in this study was 320 ppm in complete feed, or 46 to 54 mg/kg body weight/day. This is about 35 times the maximum human recommended dose of 8 mg once daily based on surface area.

Glimepiride was non-mutagenic in a battery of in vitro and in vivo mutagenicity studies (Ames test, somatic cell mutation, chromosomal aberration, unscheduled DNA synthesis, mouse micronucleus test).

There was no effect of glimepiride on male mouse fertility in animals exposed up to 2500 mg/kg body weight (> 1,700 times the maximum recommended human dose based on surface area). Glimepiride had no effect on the fertility of male and female rats administered up to 4000 mg/kg body weight (approximately 4,000 times the maximum recommended human dose based on surface area).

Pregnancy

Teratogenic Effects

Pregnancy category B

Glimepiride did not produce teratogenic effects in rats exposed orally up to 4000 mg/kg body weight (approximately 4,000 times the maximum recommended human dose based on surface area) or in rabbits exposed up to 32 mg/kg body weight (approximately 60 times the maximum recommended human dose based on surface area). Glimepiride has been shown to be associated with intrauterine fetal death in rats when given in doses as low as 50 times the human dose based on surface area and in rabbits when given in doses as low as 0.1 times the human dose based on surface area. This fetotoxicity, observed only at doses inducing maternal hypoglycemia, has been similarly noted with other sulfonylureas, and is believed to be directly related to the pharmacologic (hypoglycemic) action of glimepiride.

There are no adequate and well-controlled studies in pregnant women. On the basis of results from animal studies, glimepiride tablets should not be used during pregnancy. Because recent information suggests that abnormal blood glucose levels during pregnancy are associated with a higher incidence of congenital abnormalities, many experts recommend that insulin be used during pregnancy to maintain glucose levels as close to normal as possible.

Nonteratogenic Effects

In some studies in rats, offspring of dams exposed to high levels of glimepiride during pregnancy and lactation developed skeletal deformities consisting of shortening, thickening, and bending of the humerus during the postnatal period. Significant concentrations of glimepiride were observed in the serum and breast milk of the dams as well as in the serum of the pups. These skeletal deformations were determined to be the result of nursing from mothers exposed to glimepiride.

Prolonged severe hypoglycemia (4 to 10 days) has been reported in neonates born to mothers who were receiving a sulfonylurea drug at the time of delivery. This has been reported more frequently with the use of agents with prolonged half-lives. Patients who are planning a pregnancy should consult their physician, and it is recommended that they change over to insulin for the entire course of pregnancy and lactation.

Nursing Mothers

In rat reproduction studies, significant concentrations of glimepiride were observed in the serum and breast milk of the dams, as well as in the serum of the pups. Although it is not known whether glimepiride is excreted in human milk, other sulfonylureas are excreted in human milk. Because the potential for hypoglycemia in nursing infants may exist, and because of the effects on nursing animals, glimepiride should be discontinued in nursing mothers. If glimepiride is discontinued, and if diet and exercise alone are inadequate for controlling blood glucose, insulin therapy should be considered (see above Pregnancy, Nonteratogenic Effects).

Pediatric Use

The safety and efficacy of glimepiride were evaluated in an active-controlled, single-blind (patients only), 24 week trial involving 272 pediatric patients, ranging from 8 to 17 years of age, with Type 2 diabetes. Glimepiride (n = 135) was administered at 1 mg initially, and then titrated up to 2, 4 or 8 mg (mean last dose 4 mg) until the therapeutic goal of self-monitored fasting blood glucose < 7.0 mmol/L (< 126 mg/dL) was achieved. The active comparator metformin (n = 137) was administered at 500 mg twice daily initially and titrated up to 1000 mg twice daily (mean last dose 1365 mg).

HbA1c (%) | Naïve Patients [Intent-to-treat population (glimepiride, n = 127; metformin, n = 126)] |  | Previously Treated Patients
HbA1c (%) | Metformin | Glimepiride | Metformin | Glimepiride
HbA1c (%) | 69 | 72 | 57 | 55
Baseline (mean) | 8.2 | 8.3 | 9.0 | 8.7
Change from baseline (mean) [Change from baseline means are least square means adjusting for baseline HbA1c and Tanner Stage] | -1.2 | -1.0 | -0.2 | 0.2
Adjusted Treatment Difference [Difference is glimepiride – metformin with positive differences favoring metformin] |  | 0.2 |  | 0.4
(95% CI) |  | (-0.3; 0.7) |  | (-0.4; 1.2)

The profile of adverse reactions in pediatric patients treated with glimepiride was similar to that observed in adults.

Hypoglycemic events, as documented by blood glucose values < 36 mg/dL, were observed in 4% of patients treated with glimepiride and in 1% of patients treated with metformin.

Weight (kg) | Metformin [Safety population with on-treatment evaluation for weight (glimepiride, n = 129; metformin, n = 126)] | Glimepiride
Baseline (mean) | 67.3 | 66.5
Change from baseline (mean)) [Change from baseline means are least square means adjusting for baseline HbA1c and Tanner Stage] | 0.7 | 2.0
Adjusted Treatment Difference [Difference is glimepiride – metformin with positive differences favoring metformin] |  | 1.3
(95% CI) |  | (0.3; 2.3)

Geriatric Use

In U.S. clinical studies of glimepiride, 608 of 1986 patients were 65 and over. No overall differences in safety or effectiveness were observed between these subjects and younger subjects, but greater sensitivity of some older individuals cannot be ruled out.

Comparison of glimepiride pharmacokinetics in Type 2 diabetic patients ≤ 65 years (n = 49) and those > 65 years (n = 42) was performed in a study using a dosing regimen of 6 mg daily. There were no significant differences in glimepiride pharmacokinetics between the two age groups (see CLINICAL PHARMACOLOGY, Special Populations, Geriatric).

The drug is known to be substantially excreted by the kidney, and the risk of toxic reactions to this drug may be greater in patients with impaired renal function. Because elderly patients are more likely to have decreased renal function, care should be taken in dose selection, and it may be useful to monitor renal function.

Elderly patients are particularly susceptible to hypoglycemic action of glucose-lowering drugs. In elderly, debilitated, or malnourished patients, or in patients with renal and hepatic insufficiency, the initial dosing, dose increments, and maintenance dosage should be conservative based upon blood glucose levels prior to and after initiation of treatment to avoid hypoglycemic reactions. Hypoglycemia may be difficult to recognize in the elderly and in people who are taking beta-adrenergic blocking drugs or other sympatholytic agents (see CLINICAL PHARMACOLOGY, Special Populations, Renal Insufficiency; PRECAUTIONS, General; and DOSAGE AND ADMINISTRATION, Special Patient Population).

ADVERSE REACTIONS

Adult Patients

The incidence of hypoglycemia with glimepiride, as documented by blood glucose values < 60 mg/dL, ranged from 0.9 to 1.7% in two large, well-controlled, 1 year studies (see WARNINGS and PRECAUTIONS).

Glimepiride has been evaluated for safety in 2,013 patients in U.S. controlled trials, and in 1,551 patients in foreign controlled trials. More than 1,650 of these patients were treated for at least 1 year.

Adverse events, other than hypoglycemia, considered to be possibly or probably related to study drug that occurred in U.S. placebo-controlled trials in more than 1% of patients treated with glimepiride are shown below.

Adverse Events Occurring in > 1% Glimepiride Patients
 | Glimepiride |  | Placebo
 | No. | % | No. | %
Total Treated | 746 | 100 | 294 | 100
Dizziness | 13 | 1.7 | 1 | 0.3
Asthenia | 12 | 1.6 | 3 | 1.0
Headache | 11 | 1.5 | 4 | 1.4
Nausea | 8 | 1.1 | 0 | 0.0

Gastrointestinal Reactions

Vomiting, gastrointestinal pain, and diarrhea have been reported, but the incidence in placebo-controlled trials was less than 1%. In rare cases, there may be an elevation of liver enzyme levels. In isolated instances, impairment of liver function (e.g., with cholestasis and jaundice), as well as hepatitis, which may also lead to liver failure have been reported with sulfonylureas, including glimepiride.

Dermatologic Reactions

Allergic skin reactions, e.g., pruritus, erythema, urticaria, and morbilliform or maculopapular eruptions, occur in less than 1% of treated patients. These may be transient and may disappear despite continued use of glimepiride. If those hypersensitivity reactions persist or worsen (e.g., dyspnea, fall in blood pressure, shock), the drug should be discontinued.

Porphyria cutanea tarda, photosensitivity reactions, and allergic vasculitis have been reported with sulfonylureas, including glimepiride.

Hematologic Reactions

Leukopenia, agranulocytosis, thrombocytopenia, hemolytic anemia, aplastic anemia, and pancytopenia have been reported with sulfonylureas, including glimepiride.

Metabolic Reactions

Hepatic porphyria reactions and disulfiram-like reactions have been reported with sulfonylureas, including glimepiride. Cases of hyponatremia have been reported with glimepiride and all other sulfonylureas, most often in patients who are on other medications or have medical conditions known to cause hyponatremia or increase release of antidiuretic hormone. The syndrome of inappropriate antidiuretic hormone (SIADH) secretion has been reported with sulfonylureas, including glimepiride, and it has been suggested that certain sulfonylureas may augment the peripheral (antidiuretic) action of ADH and/or increase release of ADH.

Other Reactions

Changes in accommodation and/or blurred vision may occur with the use of glimepiride. This is thought to be due to changes in blood glucose, and may be more pronounced when treatment is initiated. This condition is also seen in untreated diabetic patients, and may actually be reduced by treatment. In placebo-controlled trials of glimepiride, the incidence of blurred vision was placebo, 0.7%, and glimepiride, 0.4%.

Pediatric Patients

In a clinical trial, 135 pediatric patients with Type 2 diabetes were treated with glimepiride. The profile of adverse reactions in these patients was similar to that observed in adults.

OVERDOSAGE

Overdosage of sulfonylureas, including glimepiride, can produce hypoglycemia. Mild hypoglycemic symptoms without loss of consciousness or neurologic findings should be treated aggressively with oral glucose and adjustments in drug dosage and/or meal patterns. Close monitoring should continue until the physician is assured that the patient is out of danger. Severe hypoglycemic reactions with coma, seizure, or other neurological impairment occur infrequently, but constitute medical emergencies requiring immediate hospitalization. If hypoglycemic coma is diagnosed or suspected, the patient should be given a rapid intravenous injection of concentrated (50%) glucose solution. This should be followed by a continuous infusion of a more dilute (10%) glucose solution at a rate that will maintain the blood glucose at a level above 100 mg/dL. Patients should be closely monitored for a minimum of 24 to 48 hours, because hypoglycemia may recur after apparent clinical recovery.

DOSAGE AND ADMINISTRATION

There is no fixed dosage regimen for the management of diabetes mellitus with glimepiride or any other hypoglycemic agent. The patient’s fasting blood glucose and HbA1c must be measured periodically to determine the minimum effective dose for the patient; to detect primary failure, i.e., inadequate lowering of blood glucose at the maximum recommended dose of medication; and to detect secondary failure, i.e., loss of adequate blood glucose lowering response after an initial period of effectiveness. Glycosylated hemoglobin levels should be performed to monitor the patient’s response to therapy.

Short-term administration of glimepiride may be sufficient during periods of transient loss of control in patients usually controlled well on diet and exercise.

Usual Starting Dose

The usual starting dose of glimepiride tablets USP as initial therapy is 1 to 2 mg once daily, administered with breakfast or the first main meal. Those patients who may be more sensitive to hypoglycemic drugs should be started at 1 mg once daily, and should be titrated carefully. (See PRECAUTIONS Section for patients at increased risk.)

No exact dosage relationship exists between glimepiride and the other oral hypoglycemic agents. The maximum starting dose of glimepiride tablets USP should be no more than 2 mg.

Failure to follow an appropriate dosage regimen may precipitate hypoglycemia. Patients who do not adhere to their prescribed dietary and drug regimen are more prone to exhibit unsatisfactory response to therapy.

Usual Maintenance Dose

The usual maintenance dose is 1 to 4 mg once daily. The maximum recommended dose is 8 mg once daily. After reaching a dose of 2 mg, dosage increases should be made in increments of no more than 2 mg at 1 to 2 week intervals based upon the patient’s blood glucose response. Long-term efficacy should be monitored by measurement of HbA1c levels, for example, every 3 to 6 months.

Glimepiride-Metformin Combination Therapy

If patients do not respond adequately to the maximal dose of glimepiride tablet USP monotherapy, addition of metformin may be considered. Published clinical information exists for the use of other sulfonylureas including glyburide, glipizide, chlorpropamide, and tolbutamide in combination with metformin.

With concomitant glimepiride tablets USP and metformin therapy, the desired control of blood glucose may be obtained by adjusting the dose of each drug. However, attempts should be made to identify the minimum effective dose of each drug to achieve this goal. With concomitant glimepiride tablets USP and metformin therapy, the risk of hypoglycemia associated with glimepiride tablets USP therapy continues and may be increased. Appropriate precautions should be taken.

Glimepiride-Insulin Combination Therapy

Combination therapy with glimepiride tablets USP and insulin may also be used in secondary failure patients. The fasting glucose level for instituting combination therapy is in the range of > 150 mg/dL in plasma or serum depending on the patient. The recommended glimepiride tablet USP dose is 8 mg once daily administered with the first main meal. After starting with low-dose insulin, upward adjustments of insulin can be done approximately weekly as guided by frequent measurements of fasting blood glucose. Once stable, combination-therapy patients should monitor their capillary blood glucose on an ongoing basis, preferably daily. Periodic adjustments of insulin may also be necessary during maintenance as guided by glucose and HbA1c levels.

Specific Patient Populations

Glimepiride tablets USP are not recommended for use in pregnancy or nursing mothers. Data are insufficient to recommend pediatric use of glimepiride tablets USP. In elderly, debilitated, or malnourished patients, or in patients with renal or hepatic insufficiency, the initial dosing, dose increments, and maintenance dosage should be conservative to avoid hypoglycemic reactions (see CLINICAL PHARMACOLOGY, Special Populations and PRECAUTIONS, General).

Patients Receiving Other Oral Hypoglycemic Agents

As with other sulfonylurea hypoglycemic agents, no transition period is necessary when transferring patients to glimepiride tablets USP. Patients should be observed carefully (1 to 2 weeks) for hypoglycemia when being transferred from longer half-life sulfonylureas (e.g., chlorpropamide) to glimepiride tablets USP due to potential overlapping of drug effect.

HOW SUPPLIED

Glimepiride tablets USP, 4 mg are blue, oval, flat bevelled edged, uncoated tablets embossed "RDY" on one side and "322" separating "3" and "22" with bisect line scoring on the other side and are supplied in bottles of 30.

Bottles of 30 - NDC # 42549-498-30

Store at 20° to 25°C (68° to 77°F) [See USP Controlled Room Temperature].

Dispense in a tight, light-resistant container as defined in the USP, with a child-resistant closure (as required).

ANIMAL TOXICOLOGY

Reduced serum glucose values and degranulation of the pancreatic beta cells were observed in beagle dogs exposed to 320 mg glimepiride/kg/day for 12 months (approximately 1,000 times the recommended human dose based on surface area). No evidence of tumor formation was observed in any organ. One female and one male dog developed bilateral subcapsular cataracts. Non-GLP studies indicated that glimepiride was unlikely to exacerbate cataract formation. Evaluation of the co-cataractogenic potential of glimepiride in several diabetic and cataract rat models was negative and there was no adverse effect of glimepiride on bovine ocular lens metabolism in organ culture.

HUMAN OPHTHALMOLOGY DATA

Ophthalmic examinations were carried out in over 500 subjects during long-term studies using the methodology of Taylor and West and Laties et al. No significant differences were seen between glimepiride and glyburide in the number of subjects with clinically important changes in visual acuity, intra-ocular tension, or in any of the five lens-related variables examined.

Ophthalmic examinations were carried out during long-term studies using the method of Chylack et al. No significant or clinically meaningful differences were seen between glimepiride and glipizide with respect to cataract progression by subjective LOCS II grading and objective image analysis systems, visual acuity, intraocular pressure, and general ophthalmic examination.

Rx Only

Manufactured by:

Dr. Reddy's Laboratories Limited
Bachepalli - 502 325 INDIA
Relabeling and Repackaging by:
STAT Rx USA LLC
Gainesville, GA 30501